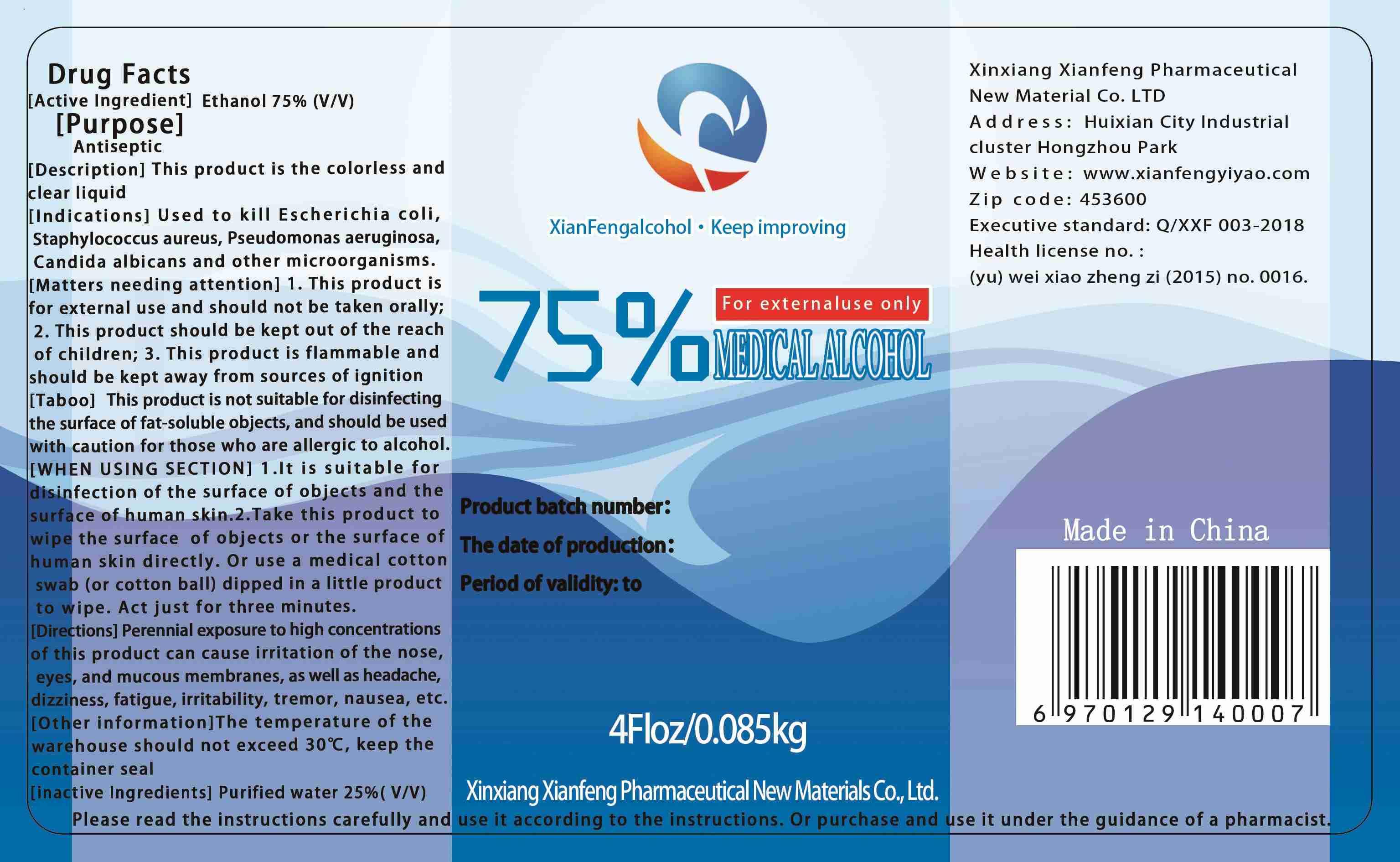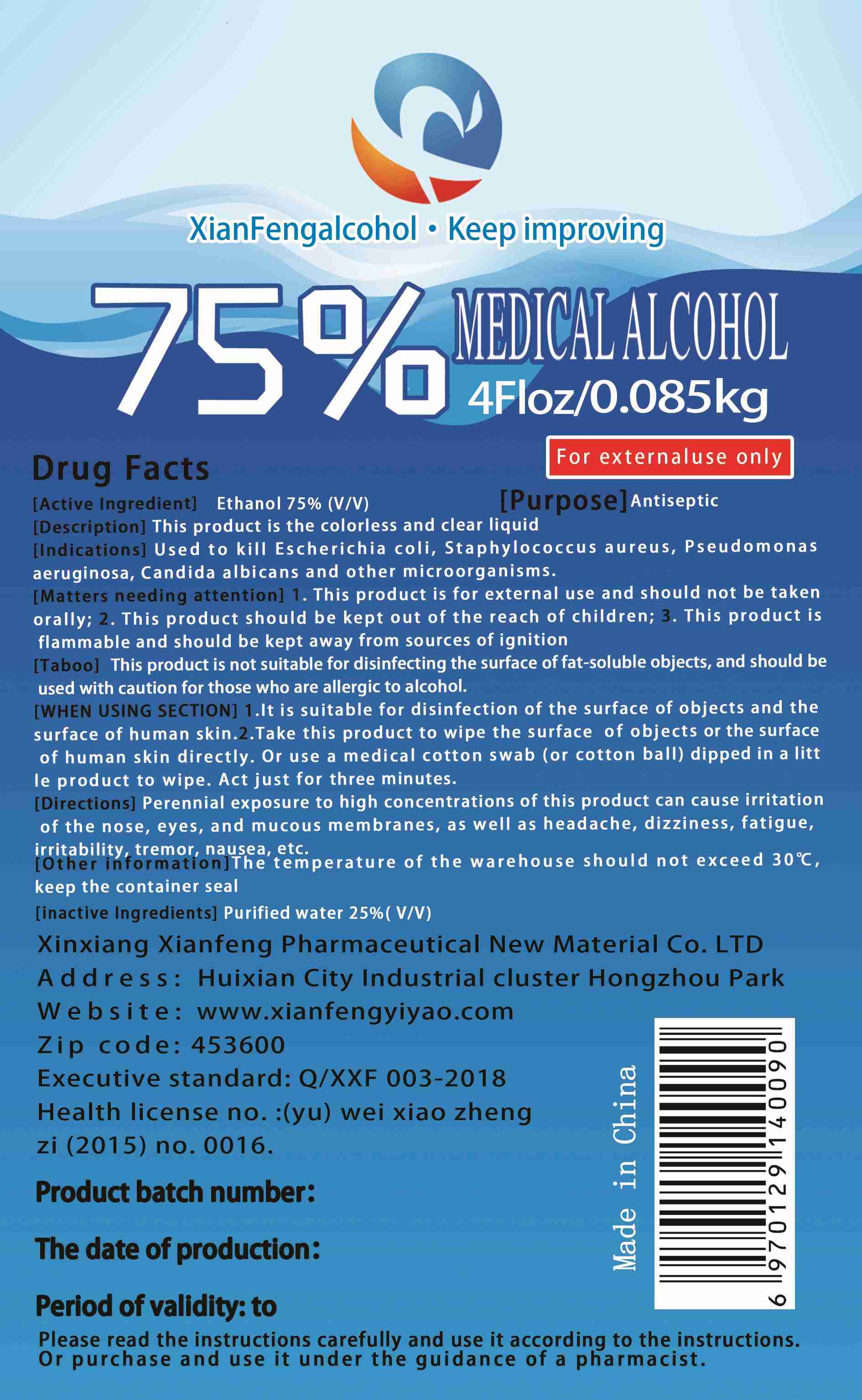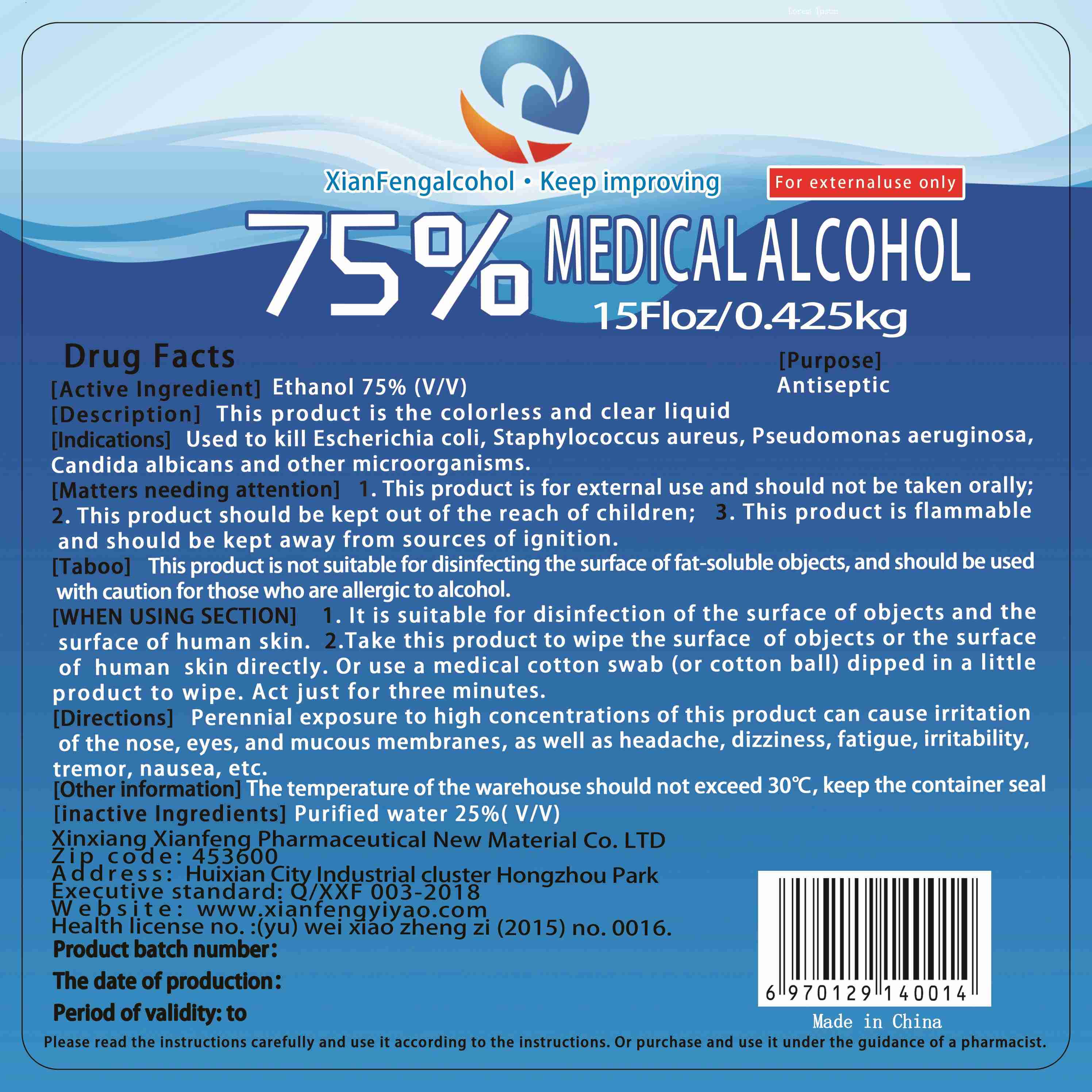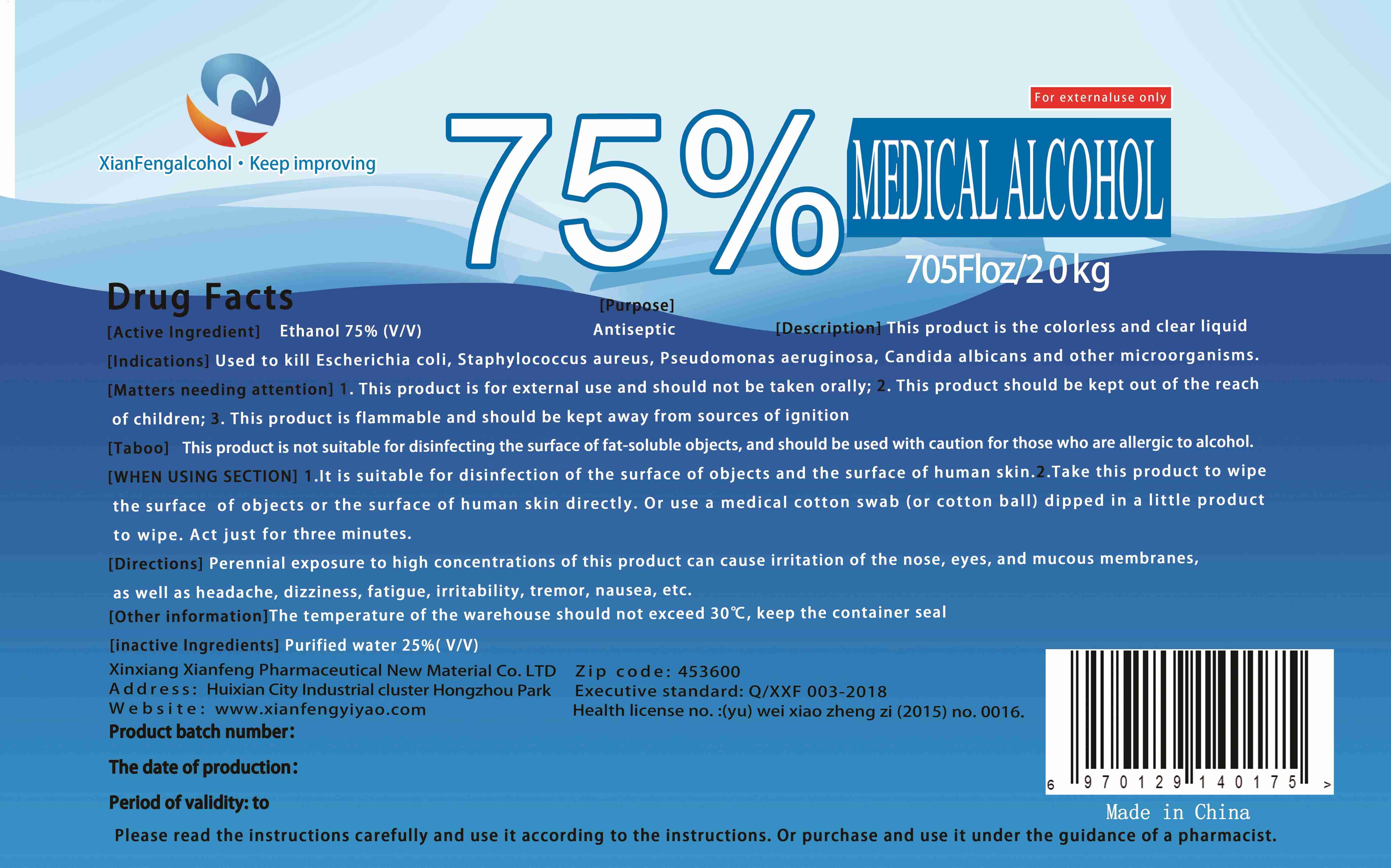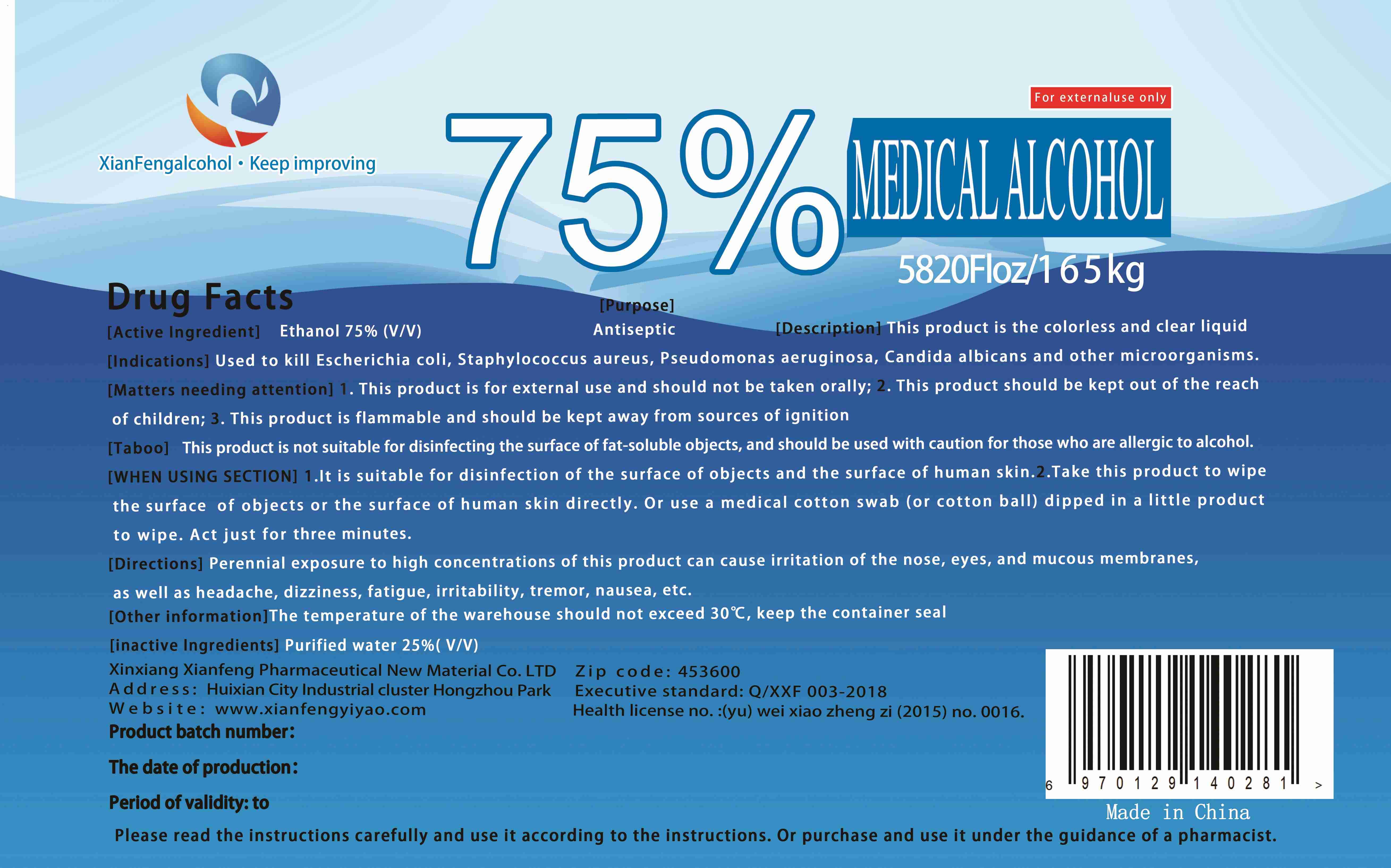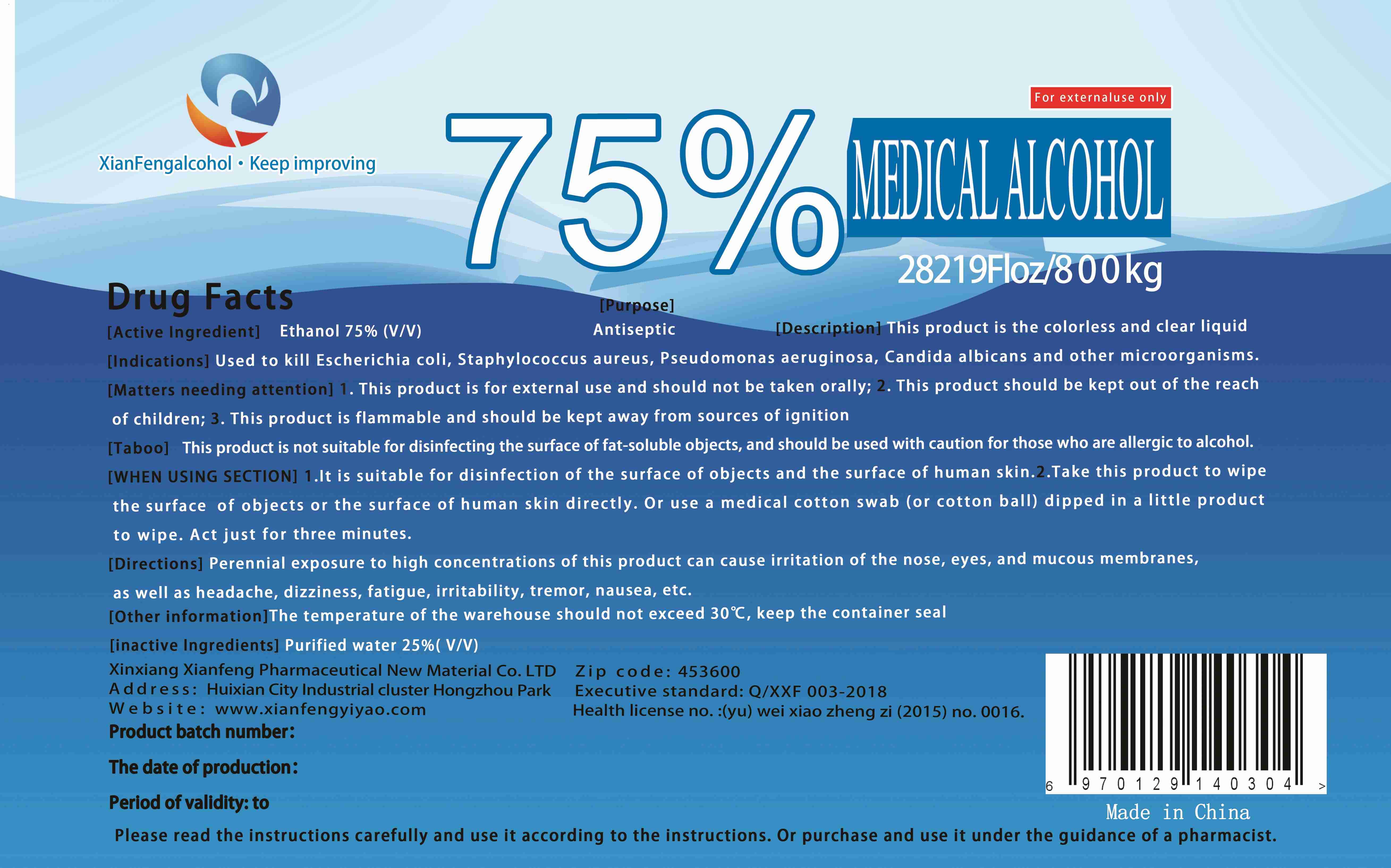 DRUG LABEL: 75% MEDICAL ALCOHOL
NDC: 80874-001 | Form: LIQUID
Manufacturer: Xinxiang Xianfeng Medicine New Material Co., Ltd.
Category: otc | Type: HUMAN OTC DRUG LABEL
Date: 20201217

ACTIVE INGREDIENTS: ALCOHOL 75 kg/100 kg
INACTIVE INGREDIENTS: WATER

80874-001
75% MEDICAL ALCOHOL

Active Ingredient(s)

Ethanol 75%(V/V)

Purpose

Antiseptic

Use

Used to kill Escherichia coli, Staphylococcus aureus, Pseudomonas aeruginosa, Candida albicans and other microorganisms.

Warnings

[Matters needing attention]
1.This product is for external use and should not be taken orally;
2.This product should be kept out of the reach of children;
3.This product is flammable and should be kept away from sources of ignition

[Taboo]
This product is not suitable for disinfecting the surface off at-soluble objects, and should be used with caution for those who are allergic to alcohol.

Do not use

/

WHEN USING

1.It is suitable for disinfection of the surface of objects and the surface of human skin.
2.Take this product to wipe the surface of objects or the surface of human skin directly.Or use a medical cotton swab(or cotton ball) dipped in a little product to wipe.Act just for three minutes.

Stop use and ask a doctor if irritation or rash occurs. These may be signs of a serious condition.

KEEP OUT OF REACH OF CHILDREN

/

Directions

Perennial exposure to high concentrations of this product can cause irritation of the nose, eyes, and mucous membranes as well as headache, dizziness, fatigue, irritability, tremor, nausea, etc.

Other information

The temperature of the warehouse should not exceed 30℃, keep the container seal

Inactive ingredients

Purified water 25%(V/V)

Package Label - Principal Display Panel

BOTTLE 80874-001-01 0.085kg

BOTTLE 80874-001-02 0.085kg

BOTTLE 80874-001-03 0.425kg

DRUM 80874-001-04 20kg

DRUM 80874-001-05 165kg

DRUM 80874-001-06 800kg